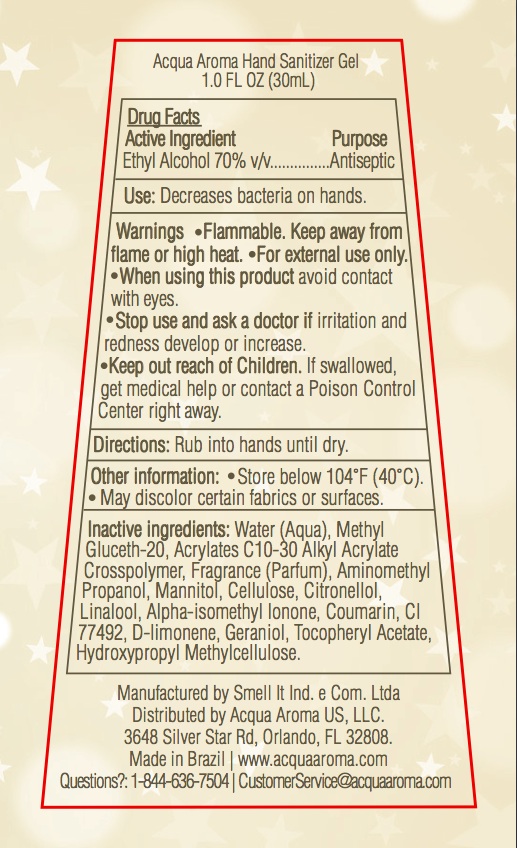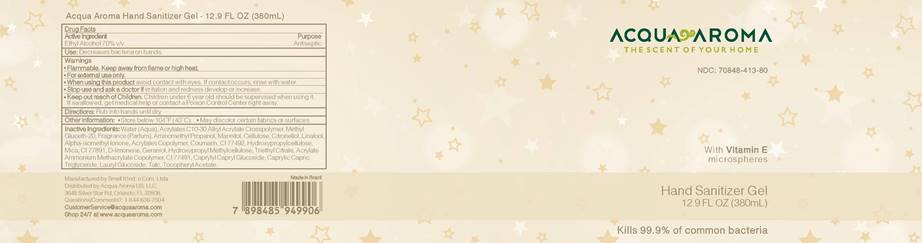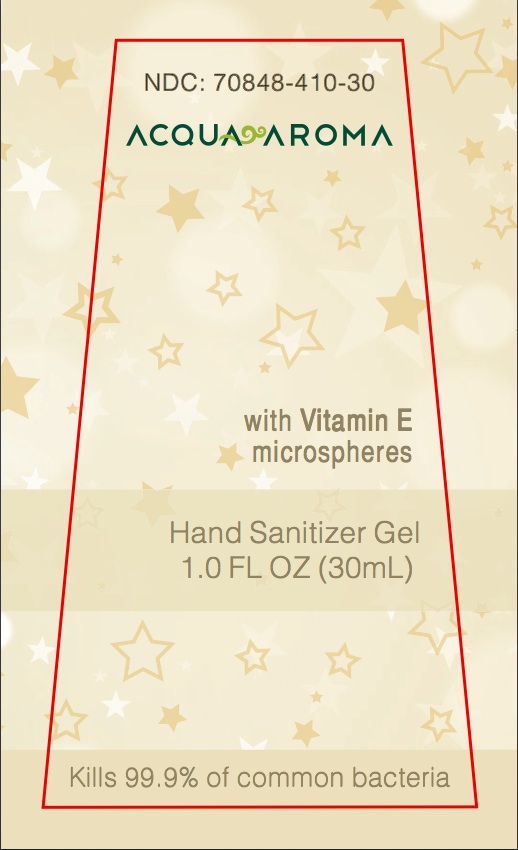 DRUG LABEL: Acqua Aroma Hand Sanitizer Gel
NDC: 70848-410 | Form: GEL
Manufacturer: Smell It Industria e Comercio Ltda
Category: otc | Type: HUMAN OTC DRUG LABEL
Date: 20200606

ACTIVE INGREDIENTS: ALCOHOL 21.024 mL/30 mL
INACTIVE INGREDIENTS: AMINOMETHYLPROPANOL 0.0315 mL/30 mL; POWDERED CELLULOSE 0.009 mL/30 mL; MANNITOL 0.0138 mL/30 mL; .ALPHA.-TOCOPHEROL ACETATE 0.00024 mL/30 mL; WATER 8.6655 mL/30 mL; CARBOMER INTERPOLYMER TYPE A (ALLYL SUCROSE CROSSLINKED) 0.09 mL/30 mL; METHYL GLUCETH-20 0.09 mL/30 mL; HYPROMELLOSES 0.00024 mL/30 mL; FERRIC OXIDE YELLOW 0.00072 mL/30 mL

Drug Facts

Active Ingredient: Ethyl Alcohol 70% v/v

Purpose:

Purpose: Antiseptic

Use

Decreases bacteria on hands.

Warnings

Flammable. Keep away from flame or high heat.

For external use only.

(For 1.0 FL OZ) Warnings:

When using this product avoid contact with eyes.

(For 12.9 FL OZ) Warnings:

When using this product avoid contact with eyes. If contact occurs, rinse with water.

Warnings

Stop use and ask a doctor if irritation and redness develop or increase.

(For 1.0 FL OZ) Warnings

Keep out reach of Children. If swallowed, get medical help or contact a Poison Control Center right away.

(For 12.9 FL OZ) Warnings:

Keep out reach of Children. Children under 6 year old should be supervised when using it. If swallowed, get medical help or contact a Poison Control Center right away.

Other Information:

Store below 104°F (40°C). May discolor certain fabrics or surfaces.

Directions

Rub into hands until dry.

(For 1.0 FL OZ) Inactive Ingredients:

Inactive ingredients: Water (Aqua), Methyl Gluceth-20, Acrylates C10-30 Alkyl Acrylate Crosspolymer, Fragrance (Parfum), Aminomethyl Propanol, Mannitol, Cellulose, Citronellol, Linalool, Alpha-isomethyl Ionone, Coumarin, CI 77492, D-limonene, Geraniol, Tocopheryl Acetate, Hydroxypropyl Methylcellulose.

(For 12.9 FL OZ) Inactive Ingredients:

Inactive Ingredients: Water (Aqua), Acrylates C10-30 Alkyl Acrylate Crosspolymer, Methyl Gluceth-20, Fragrance (Parfum), Aminomethyl Propanol, Mannitol, Cellulose, Citronellol, Linalool, Alpha-isomethyl Ionone, Acrylates Copolymer, Coumarin, CI 77492, Hydroxypropylcellulose, Mica, CI 77891, D-limonene, Geraniol, Hydroxypropyl Methylcellulose, Triethyl Citrate, Acrylate Ammonium Methacrylate Copolymer, CI 77491, Caprylyl Capryl Glucoside, Caprylic Capric Triglyceride, Lauryl Glucoside, Talc, Tocopheryl Acetate.

Questions

Questions: 1-844-636-7504 | CustomerService@acquaaroma.com

(For 1.0 OZ) Primary Panel

NDC Number Acqua Aroma With Vitamin E microspheres Hand Sanitizer Gel 1.0 FL OZ (30ML) Kills 99.9% of common bacteria

(For 12.9 OZ) Primary Panel

Acqua Aroma The Scent of Your Home NDC Number With Vitamin E microspheres Hand Sanitizer Gel 12.9 FL OZ (380ML) Kills 99.9% of common bacteria